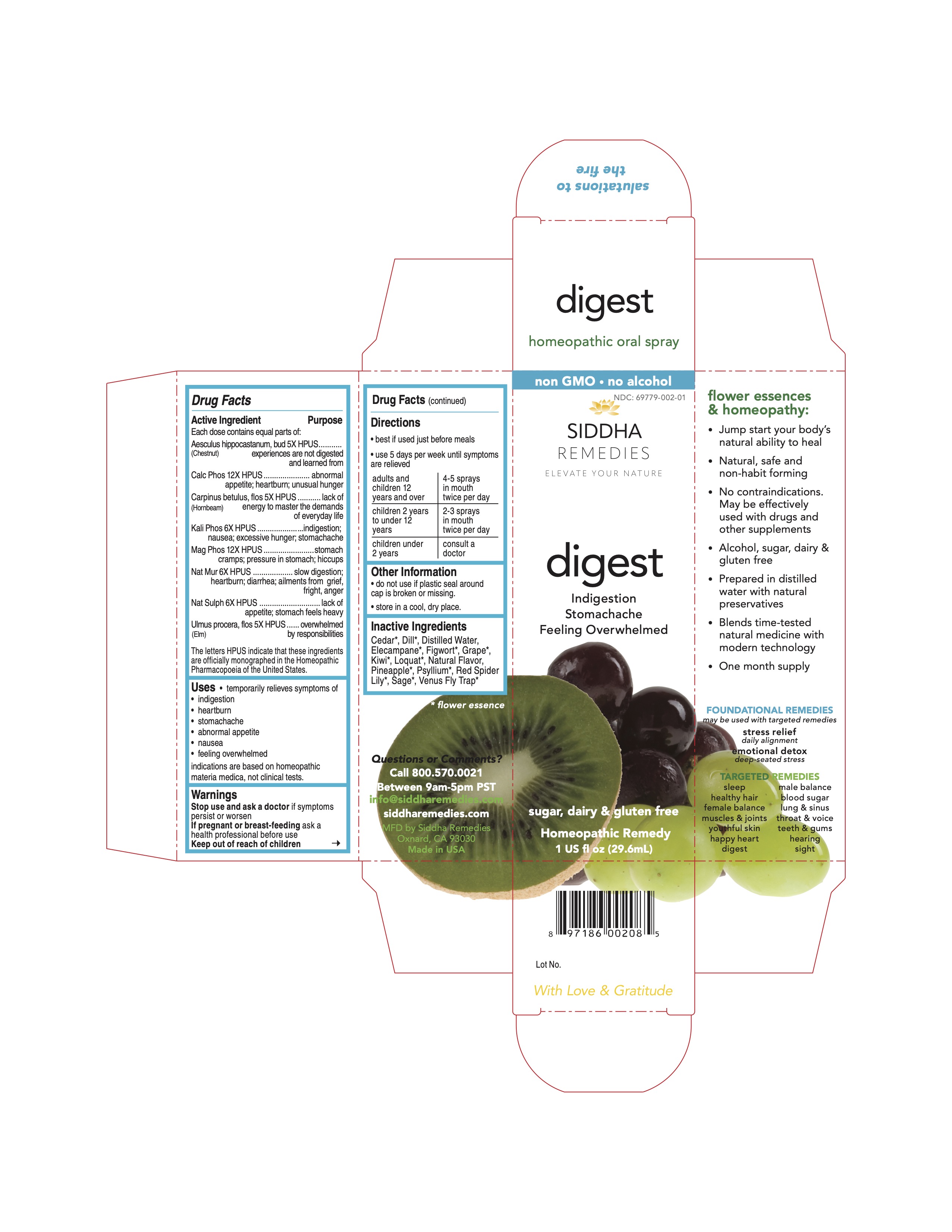 DRUG LABEL: digest
NDC: 69779-002 | Form: SPRAY
Manufacturer: Siddha Flower Essences LLC
Category: homeopathic | Type: HUMAN OTC DRUG LABEL
Date: 20251231

ACTIVE INGREDIENTS: HORSE CHESTNUT 5 [hp_X]/29.6 mL; TRIBASIC CALCIUM PHOSPHATE 12 [hp_X]/29.6 mL; POTASSIUM PHOSPHATE, DIBASIC 6 [hp_X]/29.6 mL; MAGNESIUM PHOSPHATE, DIBASIC TRIHYDRATE 12 [hp_X]/29.6 mL; SODIUM CHLORIDE 6 [hp_X]/29.6 mL; ULMUS PROCERA FLOWERING TWIG 5 [hp_X]/29.6 mL; CARPINUS BETULUS FLOWERING TOP 5 [hp_X]/29.6 mL
INACTIVE INGREDIENTS: DILL; SCROPHULARIA NODOSA; VITIS VINIFERA FLOWERING TOP; WATER; GREVILLEA SPECIOSA FLOWER

Drug Facts

Active Ingredient

Each dose contains equal parts of:
Aesculus hippocastanum, bud (Chestnut Bud) 5X HPUS
Calc Phos 12X HPUS
Carpinus betulus, flos (Hornbeam) 5X HPUS
Kali Phos 6X HPUS
Mag Phos 12X HPUS
Nat Mur 6X HPUS
Nat Sulph 6X HPUS
Ulmus procera, flos (Elm) 5X HPUS

Purpose

Each dose contains equal parts of:
Aesculus hippocastanum, bud (Chestnut Bud) 5X HPUS.....................experiences are not digested and learned from
Calc Phos 12X HPUS.......................................................................abnormal appetite; heartburn; unusual hunger
Carpinus betulus, flos (Hornbeam) 5X HPUS......................................lack of energy to master the demands of everyday life
Kali Phos 6X HPUS.........................................................................indigestion; nausea; excessive hunger; stomachache
Mag Phos 12X HPUS......................................................................stomach cramps; pressure in stomach; hiccups
Nat Mur 6X HPUS...........................................................................slow digestion; heartburn; diarrhea; ailments from grief, fright, anger
Nat Sulph 6X HPUS........................................................................lack of appetite; stomach feels heavy
Ulmus procera, flos (Elm) 5X HPUS..................................................overwhelmed by responsibilities

The letters HPUS indicate that these ingredients are officially monographed in the Homeopathic Pharmacopoeia of the United States.

INDICATIONS AND USAGE

- temporarily relieves symptoms of
- indigestion
- heartburn
- stomachache
- abnormal appetite
- nausea
- feeling overwhelmed

indications are based on homeopathic materia medica, not clinical tests.

Stop use and ask a doctor if symptoms persist or worsen

PREGNANCY OR BREAST FEEDING

If pregnant or breast-feeding ask a health professional before use

Keep out of reach of children.

DOSAGE AND ADMINISTRATION

- best if used just before meals
- use 5 days per week until symptoms are relieved

adults and children 12 years and over | 4-5 sprays in mouth twice per day
children 2 years to under 12 years | 2-3 sprays in mouth twice per day
children under 2 years | consult a doctor

Other Information

- do not use if plastic seal around cap is broken or missing.
- store in a cool, dry place.

Inactive Ingredients

Cedar*, Dill*, Elecampane*, Figwort*, Grape*, Kiwi*, Loquat*, Natural Flavor, Pineapple*, Psyllium*, Purified Water, Red Spider Lily*, Sage*, Venus Fly Tray*

*flower essence

Questions or Comments?
Call 800.570.0021
Between 9am-5pm PST
info@siddhaflowers.com
siddhaflowers.com

MFD by Siddha Flower Essences

Oxnard, CA 93030

Made in USA

Side Panel

flower essences and homeopathy:

- Jump start your body's natural ability to heal
- Natural, safe and non-habit forming
- No contraindications. May be effectively used with drugs and other supplements
- Alcohol, sugar, diary, and gluten free
- Prepared in purified water with natural preservatives
- Blends time-tested natural medicine with modern technology
- One month supply

FOUNDATIONAL REMEDIES
may be used with targeted remedies

stress relief
daily alignment
emotional detox
deep-seated stress

TARGETED REMEDIES

sleep male balance

healthy hair blood sugar

female balance lungs and sinus

muscles and joints throat and voice

youthful skin teeth and gums

happy heart hearing

digest sight

Principal Display Panel

non GMO - no alcohol

digest

Indigestion
Stomachache
Feeling Overwhelmed

sugar, dairy and gluten free

Homeopathic Remedy
1 US fl oz (29.6mL)